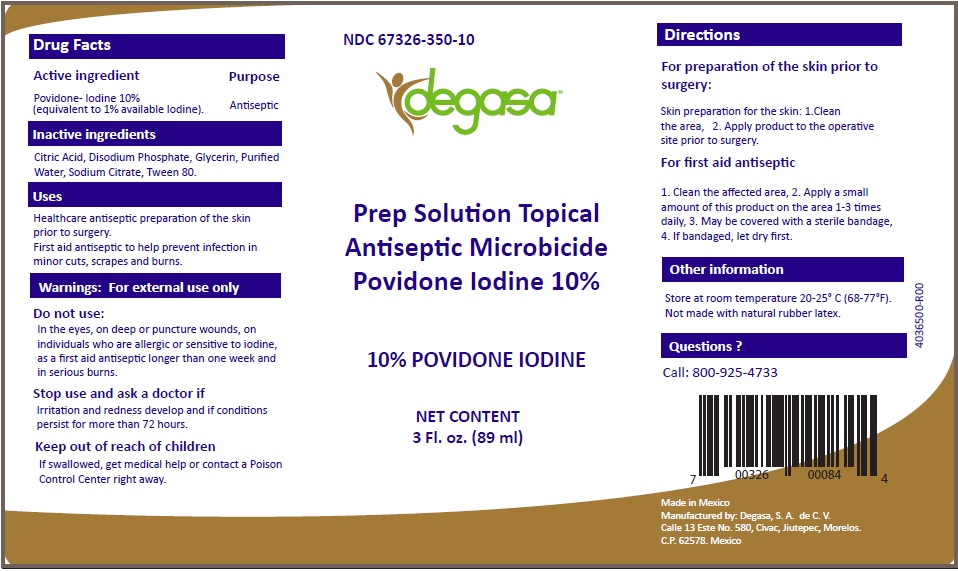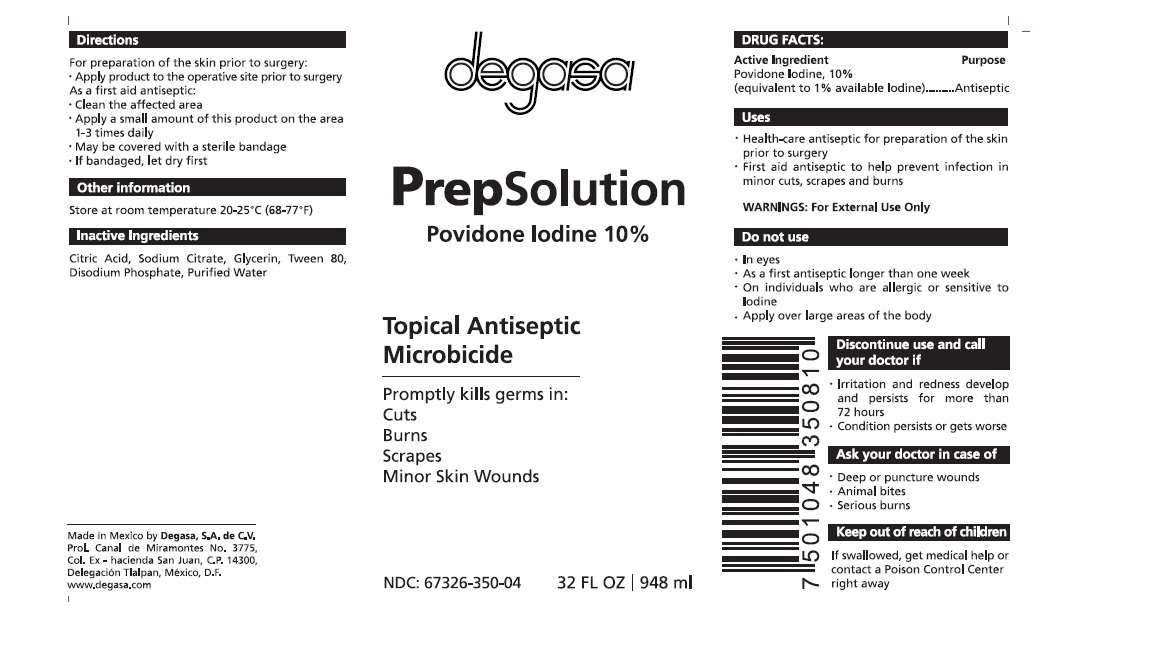 DRUG LABEL: 
                  Prep Solution
                
                  

NDC: 67326-350 | Form: SOLUTION
Manufacturer: Degasa SA De CV
Category: otc | Type: HUMAN OTC DRUG LABEL
Date: 20231105

ACTIVE INGREDIENTS: POVIDONE-IODINE 100 mg/1 mL
INACTIVE INGREDIENTS: CITRIC ACID MONOHYDRATE; SODIUM PHOSPHATE, DIBASIC, ANHYDROUS; GLYCERIN; WATER; SODIUM CITRATE; POLYSORBATE 80

Prep Solution Topical Antiseptic Microbicide

Active Ingredient

Povidone- Iodine, 10% (equivalent to 1% available Iodine).

Purpose

Antiseptic

Inactive ingredients

Citric Acid, Disodium Phosphate, Glycerin, Purified Water, Sodium Citrate, Tween 80.

Uses

Healthcare antiseptic for preparation of the skin prior to surgery. First aid antiseptic to help prevent infection in minor cuts, scrapes and burns.

Warnings:

For external use only

Do not use:

In the eyes, on deep or puncture wounds, on individuals who are allergic or sensitive to iodine, as a first aid antiseptic longer than one week and in serious burns.

Stop use and ask a doctor if

Irritation and redness develop and if conditions persist for more than 72 hours.

Keep out of reach of children

If swallowed, get medical help or contact a Poison Control Center right away.

Directions

For preparation of the skin prior to surgery:

Skin preparation for the skin: 1.Clean the area, 2. Apply product to the operative site prior to surgery.

For first aid antiseptic

1. Clean the affected area, 2. Apply a small amount of the product on the area 1-3 times daily, 3. May be covered with a sterile bandage, 4. If bandaged, let dry first.

Other information

Store at room temperature 20-25° C (68-77°F). Not made with natural rubber latex.

Questions?

Call: 800-925-4733